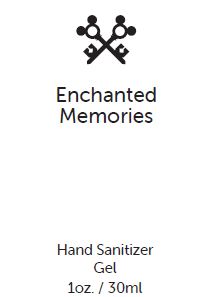 DRUG LABEL: Enchanted Memories
NDC: 80384-012 | Form: GEL
Manufacturer: SCENT FOR GOOD LLC
Category: otc | Type: HUMAN OTC DRUG LABEL
Date: 20210610

ACTIVE INGREDIENTS: ALCOHOL 60 g/100 mL
INACTIVE INGREDIENTS: WATER; METHYL GLUCETH-20; GLYCERETH-7 TRIACETATE; GLYCERIN; ALOE VERA LEAF; HYDROLYZED JOJOBA ESTERS (ACID FORM); CARBOMER INTERPOLYMER TYPE A (ALLYL SUCROSE CROSSLINKED); AMINOMETHYLPROPANOL

Enchanted Memories Hand Sanitizer

Active Ingredients:

Ethyl Alcohol 60%.

Purpose:

Antimicrobial

Use:

When soap and water are not available. This product helps reduce bacteria on your skin.

Warnings:

For external use only. Flammable. Keep away from heat or flame.

Do not use

on children less than 2 months of age or on open skin wounds.

When using this product

keep out of eyes, ears, and mouth. In case of contact with eyes, rinse eyes thoroughly with water.

Stop use and ask a doctor

if irritation or rash occurs. These may be signs of a serious condition.

Keep out of reach of children.

If swallowed, get medical help or contact a Poison Control Center immediately.

Directions:

Place enough product in palm to cover hands. Rub together until dry. Supervise children under 6 years of age when using.

Other information:

Store between 15o-30o C (59o-86o F). Avoid freezing and excessive heat above 40oC (104oF). May discolor certain fabrics or surfaces.

Inactive ingredients:

Water (Aqua), Methyl Gluceth-20, Fragrance (Parfum), Glycereth-7 Triacetate, Glycerin, Aloe Barbadensis Leaf Juice, Hydrolyzed Jojoba Esters, Acrylates/C10-30 Alkyl Acrylate Crosspolymer, Aminomethyl Propanol

PACKAGE/LABEL PRINCIPAL DISPLAY PANEL

Enchanted
Memories

Hand Sanitizer
Gel
1oz. / 30ml

80384-012-04 HAND SANITIZER.

www.scentforgood.com
@scentforgood
Manufactured by FMI for Scent for Good,
New York, NY 10011

Label